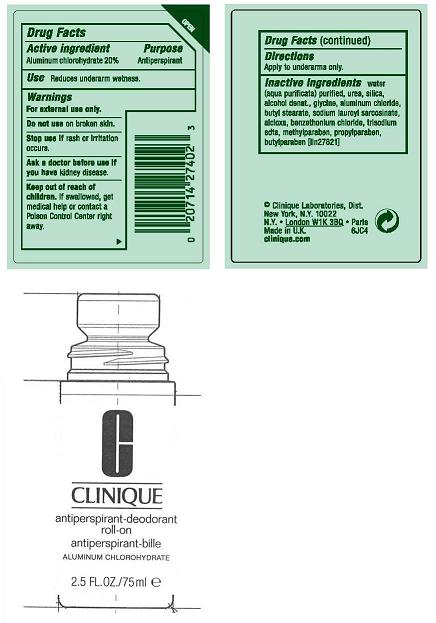 DRUG LABEL: CLINIQUE ANTIPERSPIRANT
NDC: 49527-571 | Form: LIQUID
Manufacturer: CLINIQUE LABORATORIES INC
Category: otc | Type: HUMAN OTC DRUG LABEL
Date: 20100409

ACTIVE INGREDIENTS: ALUMINUM CHLOROHYDRATE 70 mL/100 mL

ACTIVE INGREDIENT:ALUMINUM CHLOROHYDRATE 20.00%

PURPOSE

USES: DECREASES UNDERARM PERSPIRATION

WARNINGS:

- FOR EXTERNAL USE ONLY
- DO NOT USE ON BROKEN SKIN
- STOP USE IF RASH OR IRRITATION OCCURS
- ASK A DOCTOR BEFORE USE IF YOU HAVE KIDNEY DISEASE

KEEP OUT OF REACH OF CHILDREN. IF SWALLOWED, GET MEDICAL HELP OR CONTACT A POISON CONTROL CENTER RIGHT AWAY.

INDICATIONS AND USAGE

DIRECTIONS: APPLY TO UNDERARMS ONLY.

INACTIVE INGREDIENT

inactive ingredients: water[] urea [] silica [] alcohol denat. [] glycine [] aluminum chloride [] butyl stearate [] sodium lauroyl sarcosinate [] alcloxa [] benzethonium chloride [] trisodium edta [] methylparaben [] propylparaben [] butylparaben iln27821

PACKAGE LABEL

PRINCIPAL DISPLAY PANEL:

CLINIQUE
anti-perspirant deodorant roll-on
ALUMINUM CHLOROHYDRATE
2.5FL OZ./ 70ML
CLINIQUE LABORATORIES, DIST.
NEW YORK, NY 10022
6183
CLINIQUE.COM